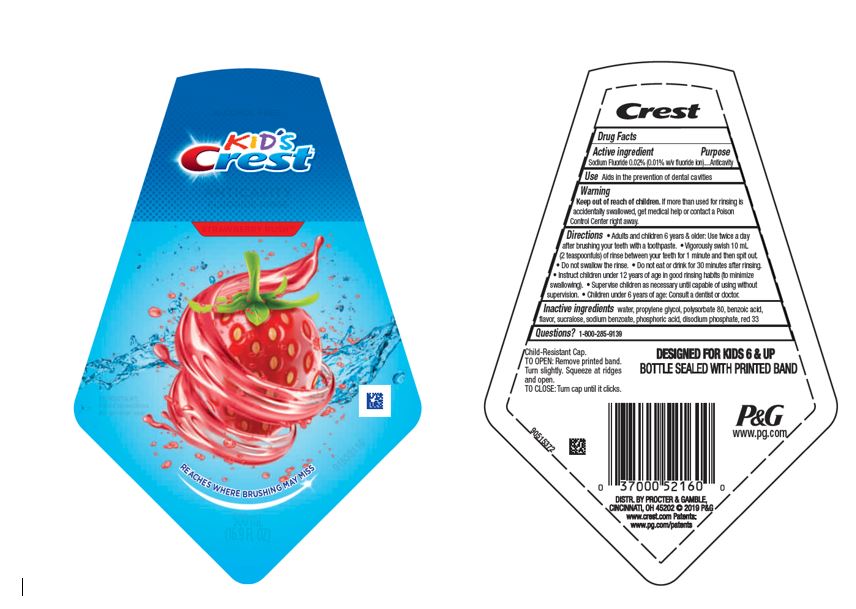 DRUG LABEL: Kids Crest
NDC: 69423-895 | Form: RINSE
Manufacturer: The Procter & Gamble Manufacturing Company
Category: otc | Type: HUMAN OTC DRUG LABEL
Date: 20250731

ACTIVE INGREDIENTS: SODIUM FLUORIDE 0.1 mg/1 mL
INACTIVE INGREDIENTS: BENZOIC ACID; PHOSPHORIC ACID; WATER; PROPYLENE GLYCOL; POLYSORBATE 80; SODIUM BENZOATE; SODIUM PHOSPHATE, DIBASIC, ANHYDROUS; SUCRALOSE; D&C RED NO. 33

Kid's Crest Strawberry Rush Anti Cavity Fluoride Rinse

Drug Facts

Active ingredient

Sodium Fluoride 0.02% (0.01% w/v fluoride ion)

Purpose

Anticavity

Use

Aids in the prevention of dental cavities

Warning

Keep out of reach of children. If more than used for rinsing is accidentally swallowed, get medical help or contact a Poison Control Center right away.

Directions

- Adults and children 6 years & older: Use twice a day after brushing your teeth with a toothpaste.
- Vigorously swish the 10 mL (2 teaspoonfuls) of rinse between your teeth for 1 minute and then spit out.
- Do not swallow the rinse.
- Do not eat or drink for 30 minutes after rinsing.
- Instruct children under 12 years of age in good rinsing habits (to minimize swallowing).
- Supervise children as necessary until capable of using without supervision.
- Children under 6 years of age: Consult a dentist or doctor.

Inactive ingredients

water, propylene glycol, polysorbate 80, benzoic acid, flavor, sucralose, sodium benzoate, phosphoric acid, disodium phosphate, red 33

Questions?

1-800-285-9139

DISTR. BY PROCTER & GAMBLE,
CINCINNATI, OH 45202

PRINCIPAL DISPLAY PANEL - 500 mL Bottle Label

ALCOHOL FREE

KID'S

Crest®
ANTICAVITY

FLUORIDE RINSE

STRAWBERRY RUSH

IMPORTANT:

Read directions

for proper use.
REACHES WHERE BRUSHING MAY MISS

500 mL

(16.9 FL OZ)